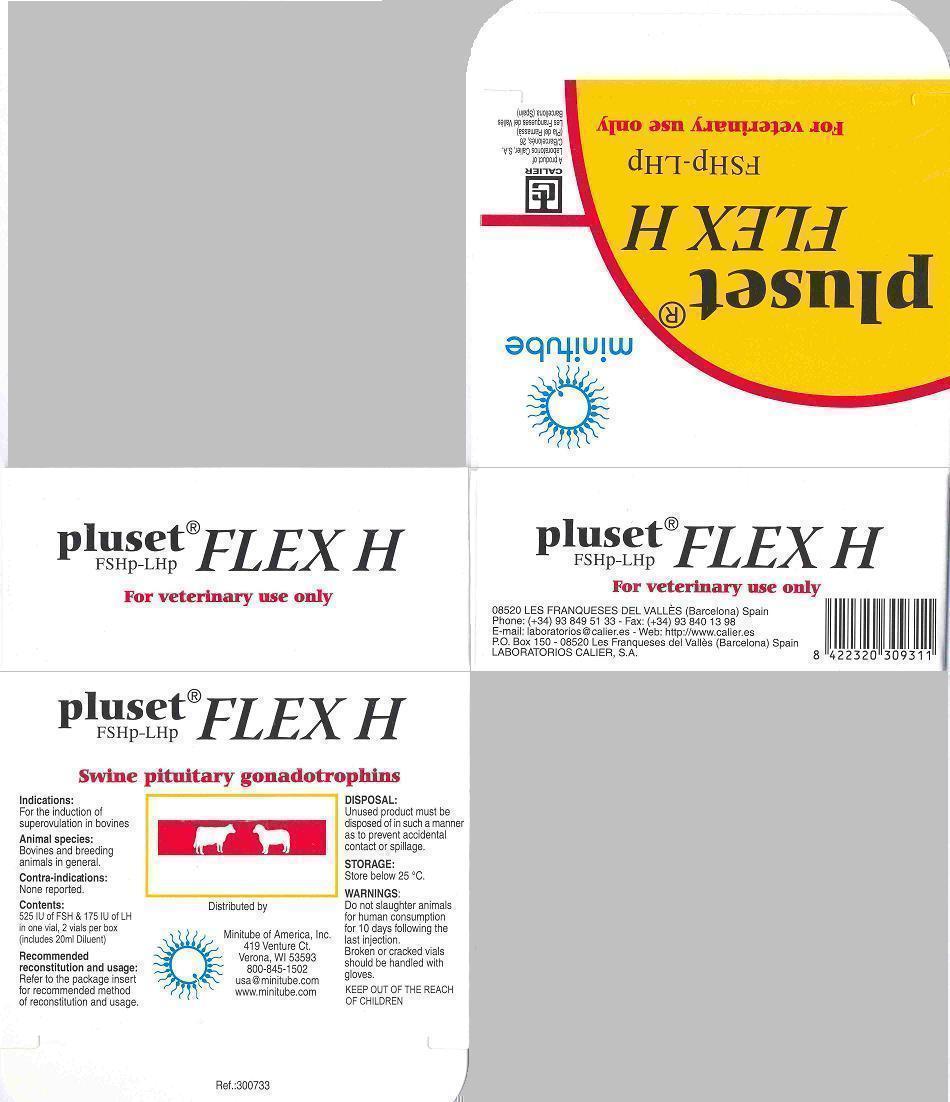 DRUG LABEL: PLUSET FLEX H
NDC: 54129-307 | Form: KIT | Route: INTRAMUSCULAR
Manufacturer: Minitube of America, Inc.
Category: animal | Type: PRESCRIPTION ANIMAL DRUG LABEL
Date: 20130516

ACTIVE INGREDIENTS: Follitropin 52.5 [iU]/1 mL; Lutropin alfa 17.5 [iU]/1 mL
INACTIVE INGREDIENTS: Sodium Chloride; Water

PLUSET FLEX H Swine pituitary gonadotrophins

DESCRIPTION

PLUSET FLEX H is a mixture of swine pituitary gonadotrophins used for the induction of multiple ovulations (superovulation). The use of standardized concentrations for both gonadotrophins guarantees a consistent quality of the product and eliminates possible variability in effectiveness from one lot to another. In the absence of an International Standard for the porcine gonadotrophin, dosing is carried out using the International Standard for human urine FSH and LH.

PROPERTIES AND ACTION

Ovarian stimulation with exogenous Follicle-Stimulating Hormone (FSH) allows a greater number of ova to be produced than normally produced in a single reproductive cycle.

The pituitary hormone extract contains variable levels of Follicle-Stimulating Hormone (FSH) and Luteinizing Hormone (LH).

Clearly in order to obtain proper and effective superovulation which provides satisfactory results involving a high number of living embryos, it is necessary to carry out a treatment that guarantees the activation and progress of multiple follicle maturation in the most "physiological" and repeatable way possible.

Thus, given that it influences the activity of FSH, it is important to have a defined level of LH present.

PLUSET FLEX H is manufactured in a method chosen to ensure that the defined level of LH content is consistently mantained.

Kinetic studies of FSH and LH in the bloodstream of bovine has shown a half-life of 150 minutes for FSH and a half-life of 40 minutes for LH.

ANIMAL SPECIES AND INDICATIONS

For the induction of superovulation in bovine females.

CONTRA-INDICATIONS

There are no ascertained contra-indications.

WARNINGS

Do not slaughter animals for human consumption for 10 days following the last injection.
Broken or cracked vials should be handled with gloves.

KEEP OUT OF THE REACH OF CHILDREN

DOSAGE AND ADMINISTRATION ROUTE

The injection of PLUSET FLEX H must be intra-muscular (i.m.). Subcutaneous administration results in an irregular absorption and must be avoided.

Reconstitute each vial of PLUSET FLEX H with 10 ml of the PLUSET diluent provided.
Reconstitution and subsequent withdrawal of product should be performed using strict aseptic technique.

Dispense the diluent into the lyophilizate bottle to completely resuspend the contents. Label the diluent bottle appropriately and mix thoroughly before use.

Regimen 1: Mature cow

Day AM PM

1 4 ml 4 ml
2 3 ml 3 ml
3 2 ml 1.5 ml
4 1.5 ml 1 ml

Regimen 2: Heifers

Day AM PM

1 3 ml 3 ml
2 2 ml 2 ml
3 1.5 ml 1.5 ml
4 1 ml 1 ml

STORAGE

The lyophilised product is stable for 24 months stored at temperature below 25 ºC. Once the preparation is prepared, the activity of the FSH and LH remain unchanged for at least six days, on condition that the preparation is stored at a temperature between 2 - 8 ºC and the normal precautions for maintaining sterility are followed.

CONTENTS

Each box contains 2 vials with 525 IU FSH/175 IU LH per vial. Includes 1 x 20 ml diluent (sterile) vial.